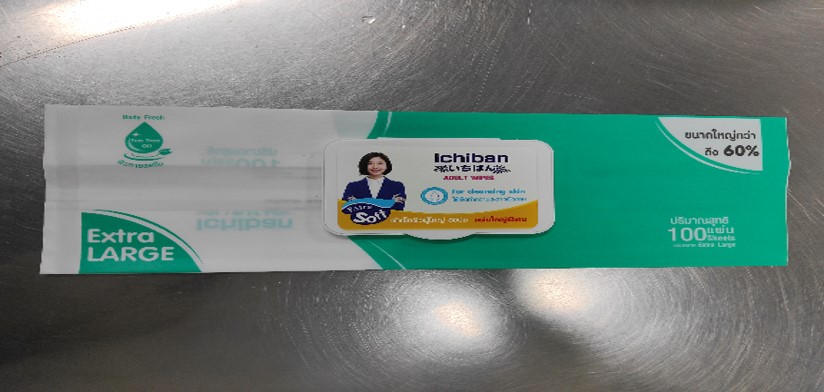 DRUG LABEL: Pet wipes
NDC: 79539-801 | Form: CLOTH
Manufacturer: Shandong Yayun Sanitary Products Co., Ltd.
Category: otc | Type: HUMAN OTC DRUG LABEL
Date: 20241120

ACTIVE INGREDIENTS: BENZALKONIUM CHLORIDE 1 g/1 1
INACTIVE INGREDIENTS: WATER; NIGERICIN; DIMETHICONOL/TRIMETHYLSILOXYSILICATE CROSSPOLYMER (40/60 W/W; 1000000 PA.S); CETRIMONIUM CHLORIDE; REBAUDIOSIDE A; DEXPANTHENOL

Pet wipes

ACTIVE INGREDIENT

Benzalkonium chloride

PURPOSE

disinfect

KEEP OUT OF REACH OF CHILDREN SECTION

INDICATIONS AND USAGE

Sanitizing wipes

WARNINGS

For external use only

DOSAGE AND ADMINISTRATION

Take out a wet wipe and wipe the desired area

INACTIVE INGREDIENT

Water
D-panthenol
Simethicone
The isodecadiol polyether
Hexadecyltrimethylammonium chloride
Alkyl glycoside